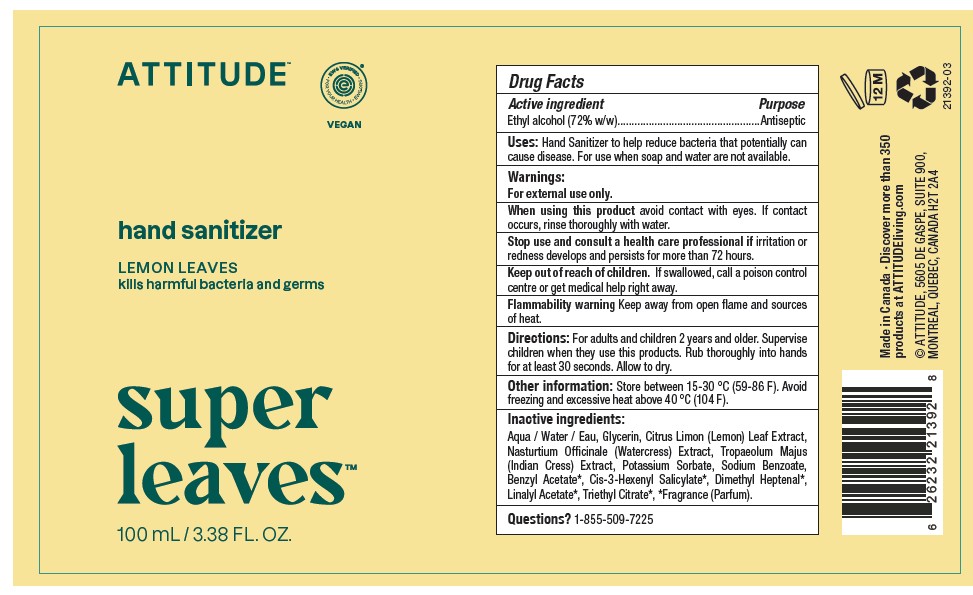 DRUG LABEL: ATTITUDE Super Leaves Hand Sanitizer Lemon Leaves
NDC: 61649-293 | Form: SOLUTION
Manufacturer: 9055-7588 Quebec Inc. DBA Attitude
Category: otc | Type: HUMAN OTC DRUG LABEL
Date: 20251020

ACTIVE INGREDIENTS: ALCOHOL 78.8 mL/100 mL
INACTIVE INGREDIENTS: GLYCERIN; TROPAEOLUM MAJUS; POTASSIUM SORBATE; 2,6-DIMETHYL-5-HEPTENAL; LINALYL ACETATE; TRIETHYL CITRATE; LEMON; NASTURTIUM OFFICINALE; WATER; BENZYL ACETATE; SODIUM BENZOATE; 3-HEXENYL SALICYLATE, CIS-

ATTITUDE Super Leaves Hand Sanitizer - Lemon Leaves

DRUG FACTS

ACTIVE INGREDIENT

Ethyl alcohol 72% (w/w)

PURPOSE

Antiseptic

INDICATIONS AND USAGE

Uses: Hand Sanitizer to help reduce bacteria that potentially can cause disease. For use when soap and water are not available.

WARNINGS

For external use only.

When using this product avoid contact with eyes. If contact occurs, rinse thoroughly with water.

Stop use and consult a health care professional if irritation or redness develops and persists for more than 72 hours.

Keep out of reach of children. If swallowed, call a poison control centre or get medical help right away.

Flammability warning. Keep away from open flame and sources of heat.

DOSAGE AND ADMINISTRATION

Directions: For adults and children 2 years and older. Supervise children when they use this products. Rub thoroughly into hands
for at least 30 seconds. Allow to dry.

Other information: Store between 15-30 °C (59-86 F). Avoid freezing and excessive heat above 40 °C (104 F).

INACTIVE INGREDIENT

Aqua / Water / Eau, Glycerin, Citrus Limon (Lemon) Leaf Extract, Nasturtium Officinale (Watercress) Extract, Tropaeolum Majus (Indian Cress) Extract, Potassium Sorbate, Sodium Benzoate, Benzyl Acetate*, Cis-3-Hexenyl Salicylate*, Dimethyl Heptenal*, Linalyl Acetate*, Triethyl Citrate*, *fragrance (Parfum).

Questions? 1-855-509-7225

PACKAGE LABEL

ATTITUDE natural care

Super Leaves

Hand sanitizer

Lemon Leaves

kills harmful bacteria and germs

EWG verified

Vegan

100 ml / 3.38 fl.oz.

Made in Canada · Discover more than 350 products at ATTITUDEliving.com

© 2023 ATTITUDE, 5605 DE GASPE, SUITE 900,
MONTREAL, QUEBEC, CANADA H2T 2A4